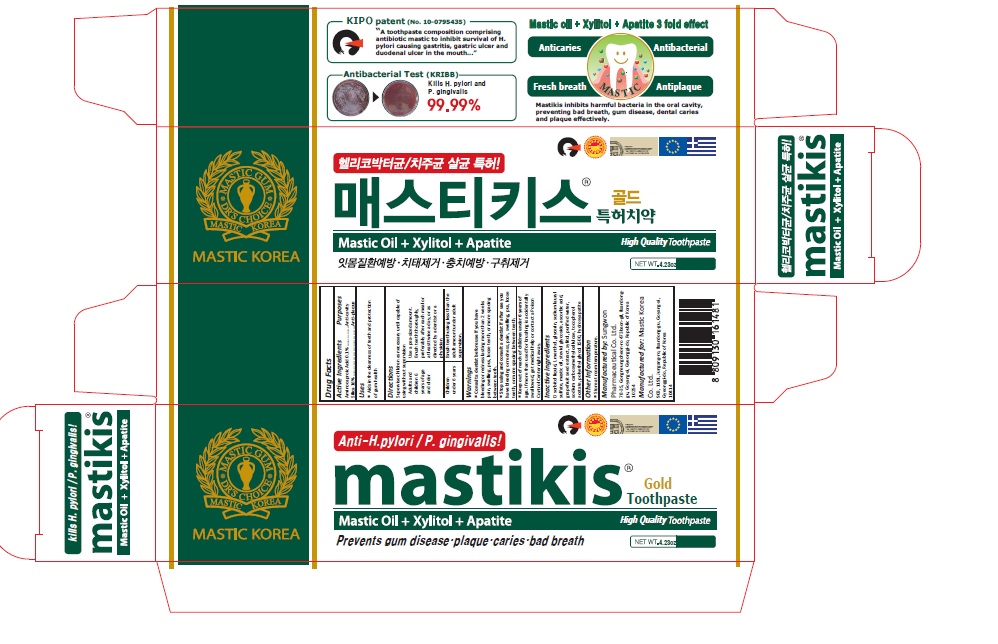 DRUG LABEL: mastikis gold
NDC: 79814-001 | Form: PASTE, DENTIFRICE
Manufacturer: Mastic Korea.Co.Ltd
Category: otc | Type: HUMAN OTC DRUG LABEL
Date: 20200731

ACTIVE INGREDIENTS: SILICON DIOXIDE 16 g/100 g; AMINOCAPROIC ACID 0.1 g/100 g
INACTIVE INGREDIENTS: SORBITOL; WATER; GLYCERIN; SODIUM LAURYL SULFATE; POLYETHYLENE GLYCOL 1600; CARBOXYMETHYLCELLULOSE SODIUM, UNSPECIFIED; CITRUS PARADISI SEED; XYLITOL; STEVIOSIDE; TRIBASIC CALCIUM PHOSPHATE; LEVOMENTHOL; ASCORBIC ACID; .ALPHA.-TOCOPHEROL ACETATE

79814-001_mastikis gold toothpaste

ACTIVE INGREDIENT

Aminocaproic Acid 0.1%
Silica 16%

INACTIVE INGREDIENT

D-Sorbitol Solution, Deionized Water, Glycerin, Mastic oil, Sodium Lauryl Sulfate, Polyethylene Glycol1500, Carboxymethylcellulose Sodium, Grapefruit Seed Extract, Xylitol, Steviol Glycoside, Hydroxyapatite, L-Menthol, Ascorbic Acid, Tocopherol Acetate

Keep out of Reach of Children.

PURPOSE

Anti-cavity

Anti-plaque

WARNINGS

If more than used for brushing is accidentally swallowed, get medical help or contact a Poison Control Center right away.

INDICATIONS AND USAGE

Aids in the cleanness of teeth and protection of gum health

DOSAGE AND ADMINISTRATION

Supervise children as necessary until capable of using without supervision.